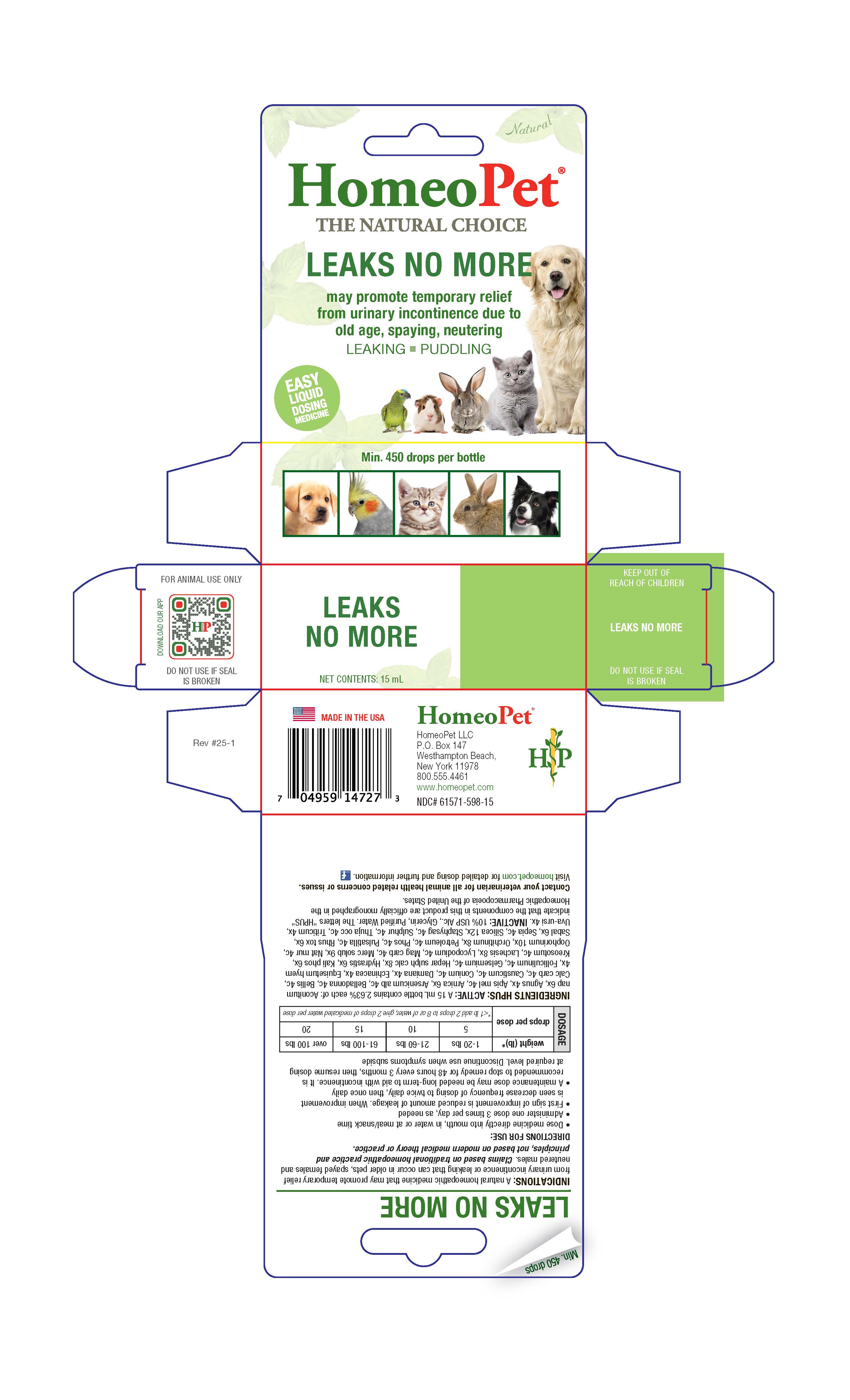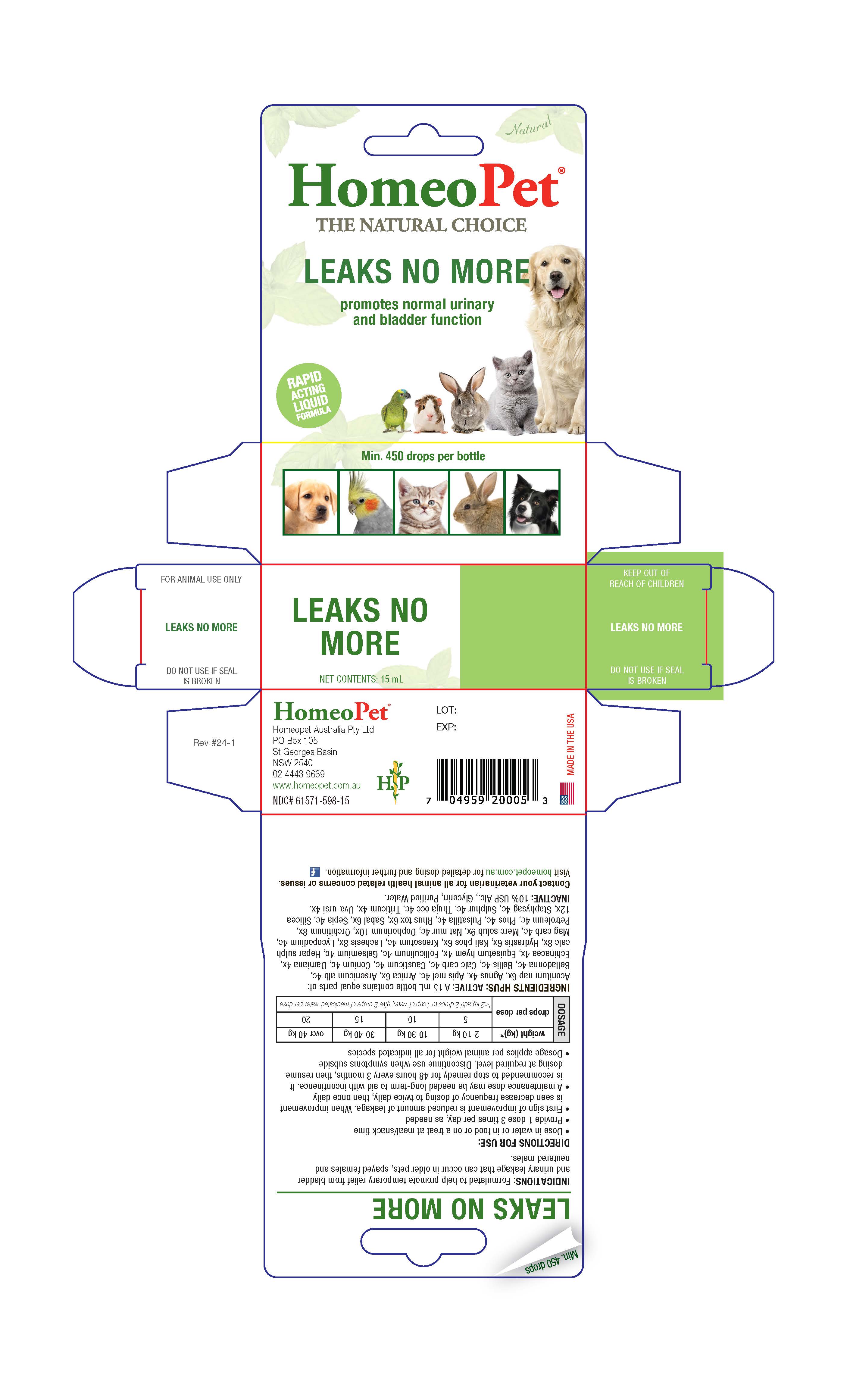 DRUG LABEL: Leaks No More
NDC: 61571-598 | Form: LIQUID
Manufacturer: HomeoPet, LLC
Category: homeopathic | Type: OTC ANIMAL DRUG LABEL
Date: 20251216

ACTIVE INGREDIENTS: ACONITUM NAPELLUS WHOLE 6 [hp_X]/15 mL; CHASTE TREE FRUIT 4 [hp_X]/15 mL; ARNICA MONTANA WHOLE 6 [hp_X]/15 mL; TURNERA DIFFUSA LEAFY TWIG 4 [hp_X]/15 mL; ECHINACEA ANGUSTIFOLIA WHOLE 4 [hp_X]/15 mL; EQUISETUM HYEMALE WHOLE 4 [hp_X]/15 mL; CALCIUM SULFIDE 8 [hp_X]/15 mL; GOLDENSEAL 6 [hp_X]/15 mL; DIBASIC POTASSIUM PHOSPHATE 6 [hp_X]/15 mL; LACHESIS MUTA VENOM 8 [hp_X]/15 mL; MERCURIUS SOLUBILIS 9 [hp_X]/15 mL; SUS SCROFA OVARY 10 [hp_X]/15 mL; BOS TAURUS TESTICLE 8 [hp_X]/15 mL; TOXICODENDRON PUBESCENS LEAF 6 [hp_X]/15 mL; SAW PALMETTO 6 [hp_X]/15 mL; SILICON DIOXIDE 12 [hp_X]/15 mL; ELYMUS REPENS ROOT 4 [hp_X]/15 mL; ARCTOSTAPHYLOS UVA-URSI LEAF 4 [hp_X]/15 mL; APIS MELLIFERA 4 [hp_C]/15 mL; ARSENIC TRIOXIDE 4 [hp_C]/15 mL; ATROPA BELLADONNA 4 [hp_C]/15 mL; BELLIS PERENNIS WHOLE 4 [hp_C]/15 mL; OYSTER SHELL CALCIUM CARBONATE, CRUDE 4 [hp_C]/15 mL; CAUSTICUM 4 [hp_C]/15 mL; CONIUM MACULATUM FLOWERING TOP 40 [hp_C]/15 mL; ESTRONE 4 [hp_C]/15 mL; GELSEMIUM SEMPERVIRENS ROOT 4 [hp_C]/15 mL; WOOD CREOSOTE 4 [hp_C]/15 mL; LYCOPODIUM CLAVATUM SPORE 4 [hp_C]/15 mL; MAGNESIUM CARBONATE 4 [hp_C]/15 mL; SODIUM CHLORIDE 4 [hp_C]/15 mL; KEROSENE 4 [hp_C]/15 mL; PHOSPHORUS 4 [hp_C]/15 mL; PULSATILLA PRATENSIS WHOLE 4 [hp_C]/15 mL; SEPIA OFFICINALIS JUICE 4 [hp_C]/15 mL; DELPHINIUM STAPHISAGRIA SEED 4 [hp_C]/15 mL; SULFUR 4 [hp_C]/15 mL; THUJA OCCIDENTALIS LEAFY TWIG 4 [hp_C]/15 mL
INACTIVE INGREDIENTS: GLYCERIN; ALCOHOL; WATER

Leaks No More

Leaks No More

may promotes temporary relief from urinary incontinence due to old age, spaying, neutering

LEAKING-PUDDLING

Contact Veterinarian

Contact your veterinarian for all animal health relaed concerns or issues.

Visit homeopet.com for detailed dosing and further information.

Ingredients HPUS: Active

Aconitum nap 6x, Agnus 4x, Apis mel 4c, Arnica 6x, Arsenicum alb 4c, Belladonna 4c, Bellis 4c, Calc carb 4c, Causticum 4c, Conium 4c, Damiana 4x, Echinacea 4x, Equisetum hyem 4x, Folliculinum 4c, Gelsemium 4c, Hepar sulph calc 8x, Hydrastis 6x, Kali phos 6x, Kreosotum 4c, Lachesis 8x, Lycopodium 4c, Mag carb 4c, Merc solub 9x, Nat mur 4c, Oophorinum 10x, Orchitinum 8x, Petroleum 4c, Phos 4c, Pulsatilla 4c, Rhus tox 6x, Sabal 6x, Sepia 4c, Silicea 12x, Staphysag 4c, Sulphur 4c, Thuja occ 4c, Triticum 4x, Uva-ursi 4x.

Inactive Ingredients

Glycerin, USP Alcohol, Purified Water

Indications

A natural homeopathic medicine that may promote temporary relief from urinary incontinence or leaking that can occur in older pets, spayed females and neutered males. Claims based on traditional homeopathic practice and principles, not based on modern medical theory or practice.

Directions for Use and Dosage

- Dose medicine directly into mouth, in water or at meal/snack time
- Administer one dose 3 times per day, as needed
- First sign of improvement is reduced amount of leakage. When improvement is seen decrease frequency of dosing to twice daily, then once daily
- A maintenance dose may be needed long-term to aid with incontinence. It is recommended to stop remedy for 48 hours every 3 months, then resume dosing at required level. Discontinue use when symptoms subside

DOSAGE

weight (lb)* | drops per dose
1-20 | 5
21-60 | 10
61-100 | 15
over 100 | 20
*<1 lb add 2 drops to 8 oz of water, give 2 drops of medicated water per dose